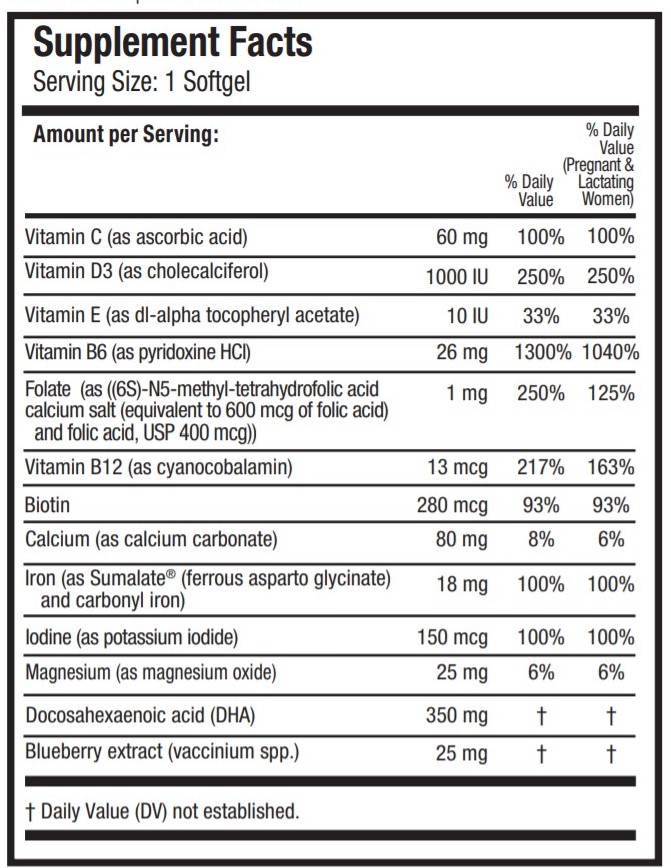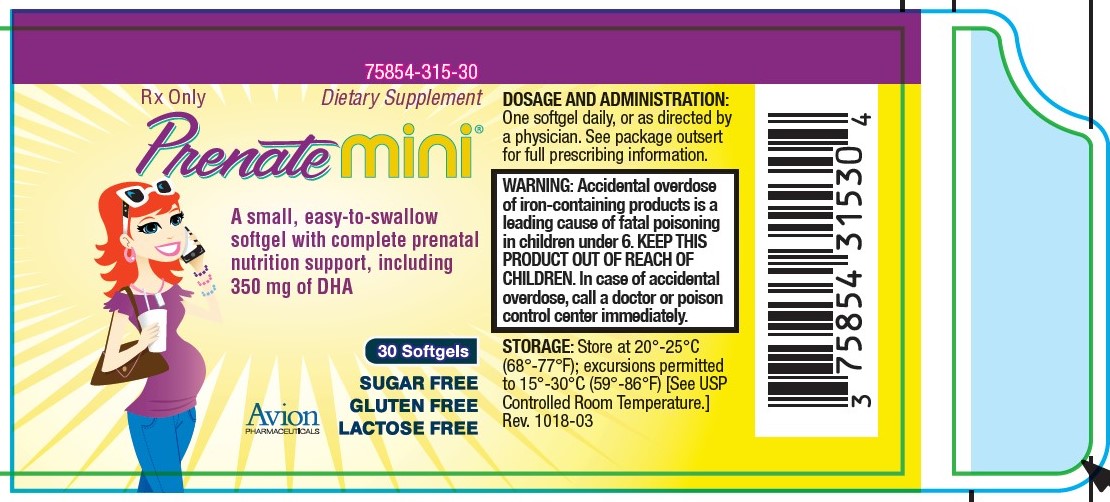 DRUG LABEL: Prenate Mini
NDC: 75854-315 | Form: CAPSULE, GELATIN COATED
Manufacturer: Avion Pharmaceuticals, LLC
Category: prescription | Type: HUMAN PRESCRIPTION DRUG LABEL
Date: 20240123

ACTIVE INGREDIENTS: BIOTIN 280 ug/1 1; CALCIUM CARBONATE 80 mg/1 1; FERROUS ASPARTO GLYCINATE 9 mg/1 1; IRON 9 mg/1 1; POTASSIUM IODIDE 150 ug/1 1; MAGNESIUM OXIDE 25 mg/1 1; DOCONEXENT 350 mg/1 1; LOWBUSH BLUEBERRY 25 mg/1 1; LEVOMEFOLIC ACID 600 ug/1 1; ASCORBIC ACID 60 mg/1 1; CHOLECALCIFEROL 1000 [iU]/1 1; .ALPHA.-TOCOPHEROL ACETATE, DL- 10 [iU]/1 1; PYRIDOXINE HYDROCHLORIDE 26 mg/1 1; FOLIC ACID 400 ug/1 1; CYANOCOBALAMIN 13 ug/1 1
INACTIVE INGREDIENTS: FISH OIL; GELATIN; GLYCERIN; LECITHIN, SOYBEAN; YELLOW WAX; WATER; CORN OIL; FD&C BLUE NO. 1; TITANIUM DIOXIDE; FD&C YELLOW NO. 5

Prenate Mini® 75854-0315-30

Rx Only Dietary Supplement

DESCRIPTION

DESCRIPTION: PRENATE MINI® is a prescription prenatal/postnatal multivitamin/mineral/essential fatty acid softgel. Each oval softgel is teal green in color and imprinted with “Mini”.

Contains fish oil and soy. Contains FD&C Yellow No. 5 (tartrazine) as a color additive.

INACTIVE INGREDIENT

OTHER INGREDIENTS: Bovine gelatin, FD&C Blue #1, FD&C Yellow #5, fish (tuna) oil, glycerin, purified water, soy lecithin, titanium dioxide, vegetable shortening and yellow beeswax.

INDICATIONS AND USAGE

INDICATIONS: PRENATE MINI® is a multivitamin/multimineral fatty acid dietary supplement indicated for use in improving the nutritional status of women throughout pregnancy and in the postnatal period for both lactating and nonlactating mothers.

PRENATEMINI® can also be beneficial in improving the nutritional status of women prior to conception.

CONTRAINDICATIONS

CONTRAINDICATIONS: PRENATE MINI® is contraindicated in patients with a known hypersensitivity to any of the ingredients.

BOXED WARNING

WARNING: Ingestion of more than 3 grams of omega-3 fatty acids (such as DHA) per day has been shown to have potential antithrombotic effects, including an increased bleeding time and International Normalized Ratio (INR). Administration of omega-3 fatty acids should be avoided in patients taking anticoagulants and in those known to have an inherited or acquired predisposition to bleeding.

PRECAUTIONS

PRECAUTIONS: Folic acid alone is improper therapy in the treatment of pernicious anemia and other megaloblastic anemias where Vitamin B12 is deficient. Folic acid in doses above 1.0 mg daily may obscure pernicious anemia in that hematologic remission can occur while neurological manifestations progress. This product contains FD&C Yellow No. 5 (tartrazine) which may cause allergic-type reactions (including bronchial asthma) in certain susceptible persons. Although the overall incidence of FD&C Yellow No. 5 (tartrazine) sensitivity in the general population is low, it is frequently seen in patients who also have aspirin hypersensitivity.

BOXED WARNING

WARNING: Accidental overdose of iron-containing products is a leading cause of fatal poisoning in children under 6. Keep this product out of reach of children. In case of accidental overdose, call a doctor or poison control center immediately.

ADVERSE REACTIONS

ADVERSE REACTIONS: Allergic sensitization has been reported following both oral and parenteral administration of folic acid.

DOSAGE AND ADMINISTRATION: Before, during and/or after pregnancy, one softgel daily or as directed by a physician.

HOW SUPPLIED

HOW SUPPLIED: Bottles of 30 softgels (75854-0315-30). The listed product number is not a National Drug Code. Instead, Avion Pharmaceuticals has assigned a product code formatted according to standard industry practice to meet the formatting requirements of pharmacy and healthcare insurance computer systems.

STORAGE AND HANDLING

STORAGE: Store at 20° - 25°C (68° - 77°F); excursions permitted to 15° - 30°C (59° - 86°F) [See USP Controlled Room Temperature.]

MANUFACTURED FOR:

Avion Pharmaceuticals, LLC

Alpharetta, GA 30005

1-888-61-AVION

Rev. 0519-01

Sumalate® is a registered trademark of Albion Laboratories,Inc., covered by one or more claims of U.S. Patent Nos. 6,716,814; 8,007,846; and 8,425,956.

PRENATE® is a registered trademark of Avion Pharmaceuticals, LLC. All rights reserved.

THESE STATEMENTS HAVE NOT BEEN EVALUATED BY THE FOOD AND DRUG ADMINISTRATION. THIS PRODUCT IS NOT INTENDED TO DIAGNOSE, TREAT, CURE OR PREVENT ANY DISEASE.

KEEP THIS AND ALL MEDICATIONS OUT OF THE REACH OF CHILDREN.

PACKAGE LABEL.PRINCIPAL DISPLAY PANEL

75854-0315-30

Rx Only Dietary Supplement

Prenate mini®

A small, easy-to-swallow
softgel with complete prenatal
nutrition support, including
350 mg of DHA

30 Softgels

SUGAR FREE

GLUTEN FREE
LACTOSE FREE

Avion
PHARMACEUTICALS